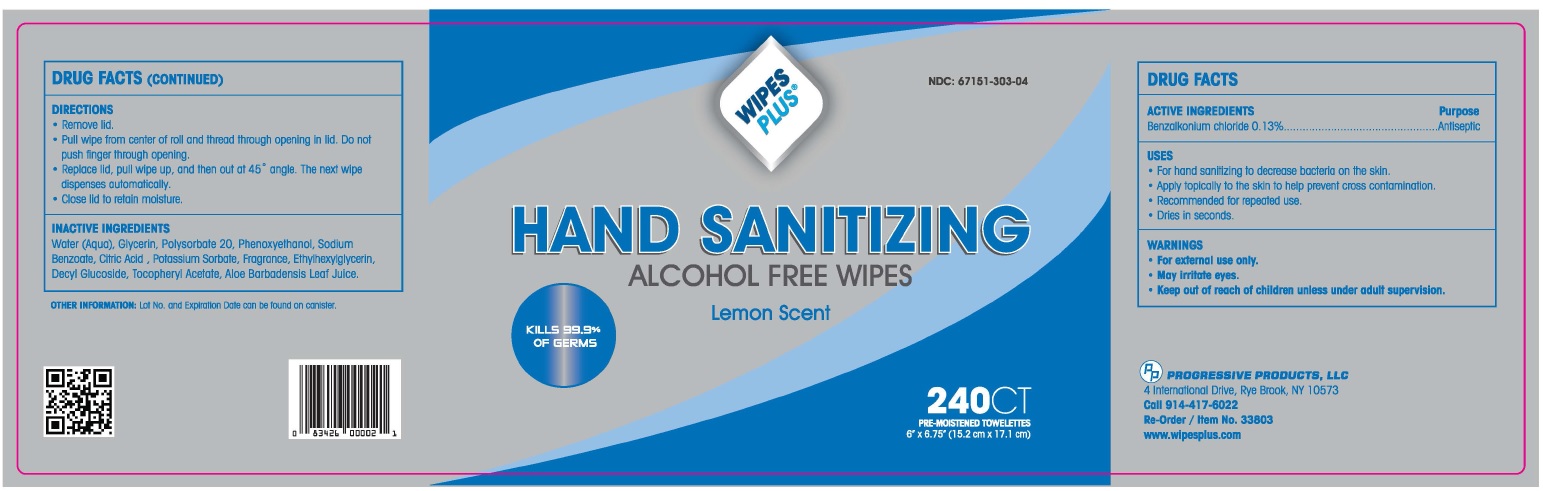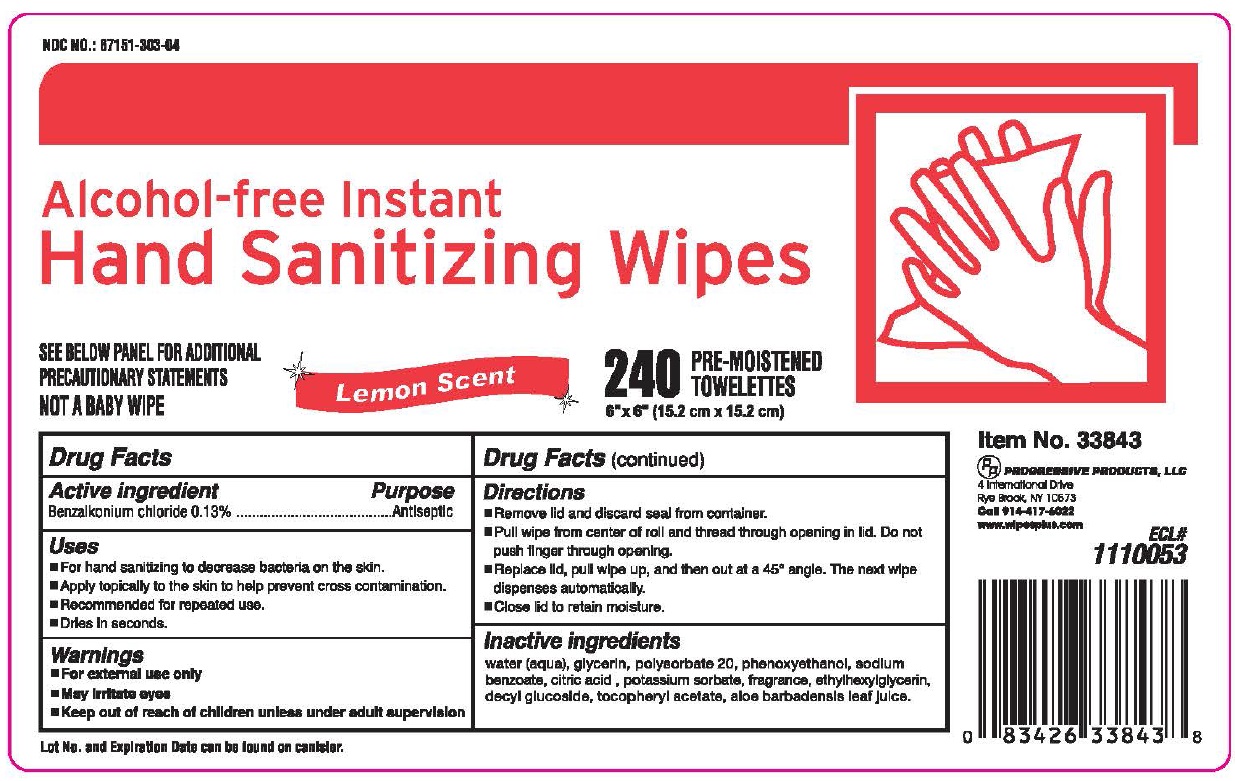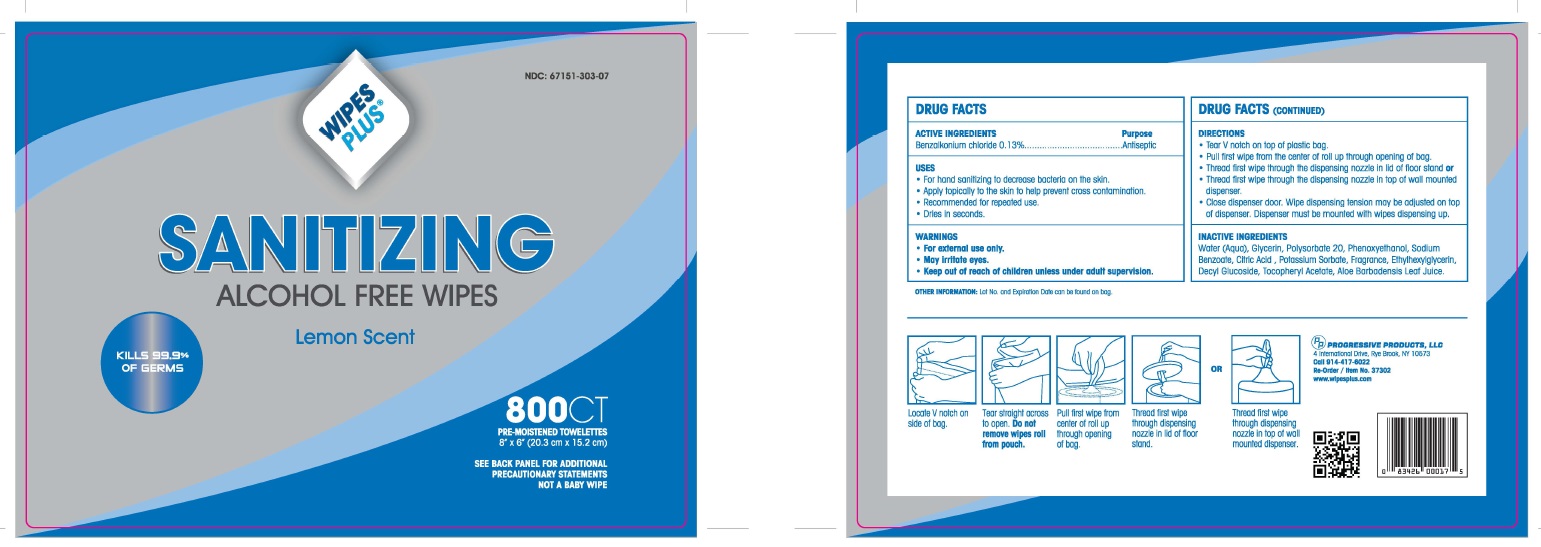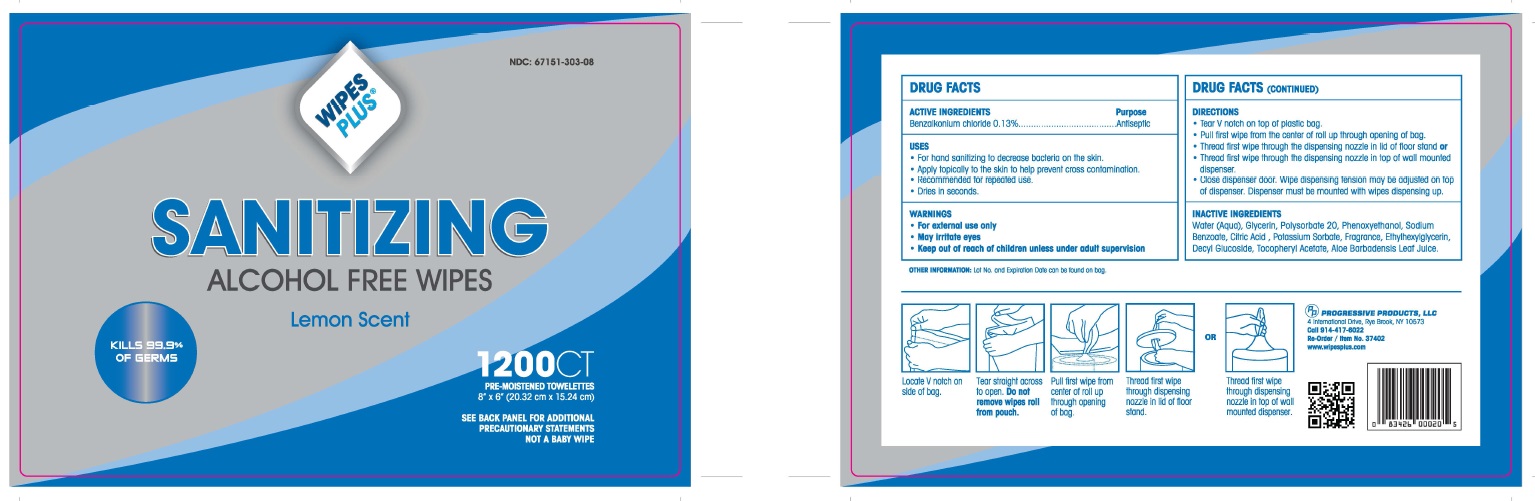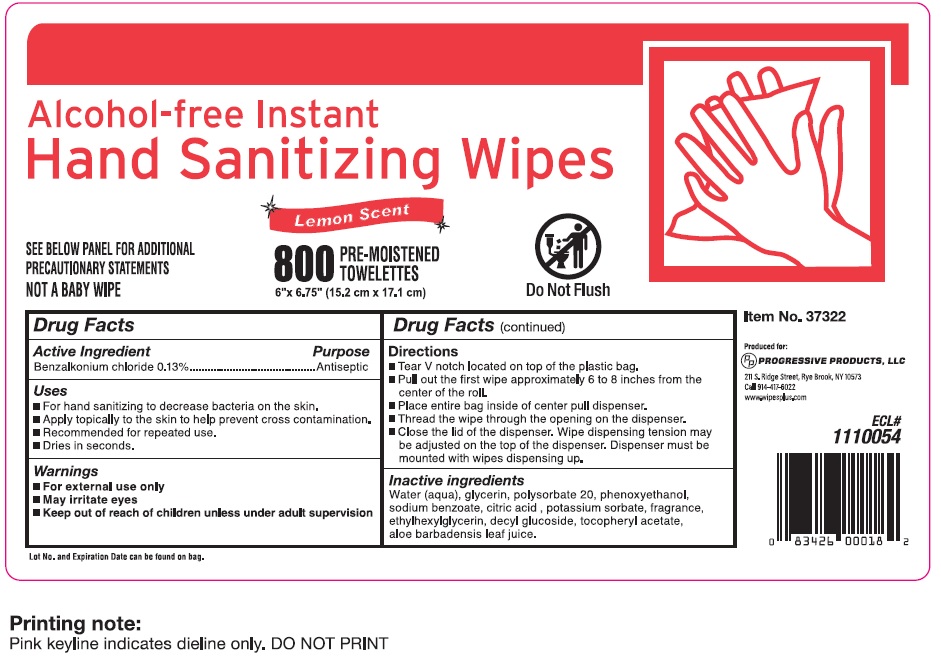 DRUG LABEL: Wipes Plus
NDC: 67151-303 | Form: SWAB
Manufacturer: Progressive Products, LLC
Category: otc | Type: HUMAN OTC DRUG LABEL
Date: 20221003

ACTIVE INGREDIENTS: BENZALKONIUM CHLORIDE 0.0062 g/1 1
INACTIVE INGREDIENTS: WATER; GLYCERIN; POLYSORBATE 20; PHENOXYETHANOL; SODIUM BENZOATE; CITRIC ACID MONOHYDRATE; POTASSIUM SORBATE; ETHYLHEXYLGLYCERIN; DECYL GLUCOSIDE; .ALPHA.-TOCOPHEROL ACETATE; ALOE VERA LEAF

DRUG FACTS

Active Ingredient

Benzalkonium chloride 0.13%

Purpose

Antiseptic

Uses

- For hand sanitizing to decrease bacteria on the skin.
- Apply topically to the skin to help prevent cross contamination.
- Recommended for repeated use.
- Dries in seconds.

Warnings

- For external use only
- May irritate eyes

Keep our of reach of children

Keep out of reach of children unless under adult supervision

Directions

- Remove lid and discard seal from container
- Pull wipe from center of roll and thread through opening in lid. Do not push finger through opening.
- Replace lid, pull wipe up, and the out at 45° angle. The next wipe dispenses automatically
- Close lid to retain moisture

OR

- Tear V notch on top of plastic bag
- Pull first wipe from the center of roll through opening of bag
- Thread first-wipe through the dispensing noozle in lid of floor stand or
- Thread first-wipe through the dispensing noozle in top of wall mounted dispenser
- Close dispenser door, Wipe dispensing tension may be adjusted on top of dispenser. Dispenser must be mounted with wipes dispensing up.

Inactive Ingredients

Water (Aqua), Glycerin, Polysorbate 20, Phenoxyethanol, Sodium Benzoate, Citric Acid, Potassium Sorbate, Fragrance, Ethylhexylglycerin, Decyl Glucoside, Tocopheryl Acetate, Aloe Barbadensis Leaf Juice.

Principal Display Panel

NDC 67151-303-01

WIPES PLUS®

Re-Order / Item No. 37503

80 CT PRE_MOISTENED TOWELETTES

6.3" X 6.7" (16 cm X 17.01 cm)

NDC 67151-303-04

WIPES PLUS®

HAND SANITIZING

ALCOHOL FREE WIPES

LEMON SCENT

KILLS 99.9% OF GERMS

240 PRE-MOISTENED TOWELETTES

6' X 6.75' (15.2 cm X 17.1 cm)

PROGRESSIVE PRODUCTS, LLC

4 International Drive, Rye Brook, NY 10573

Call 914-4176022

Re-Order / item No. 33803

www.wipesplus.com

NDC 67151-303-07

WIPES PLUS®

SANITIZING

ALCOHOL FREE WIPES

LEMON SCENT

KILLS 99.9% OF GERMS in 15 SECONDS

800 PRE-MOISTENED TOWELETTES

8" X 6" (20.3 cm X 15.2 cm)

SEE BACK PANEL FOR ADDITONAL PRECAUTIONARY STATEMENTS

NOT A BABY WIPE

PROGRESSIVE PRODUCTS, LLC

4 International Drive, Rye Brook, NY 10573

Call 914-4176022

Re-Order / item No. 33803

www.wipesplus.com

NDC 67151-303-08

WIPES PLUS®

SANITIZING

ALCOHOL FREE WIPES

LEMON SCENT

KILLS 99.9% OF GERMS in 15 SECONDS

1200 PRE-MOISTENED TOWELETTES

8" X 5" (20.32 cm X 12.7 cm)

SEE BACK PANEL FOR ADDITONAL PRECAUTIONARY STATEMENTS

NOT A BABY WIPE

PROGRESSIVE PRODUCTS, LLC

4 International Drive, Rye Brook, NY 10573

Call 914-4176022

Re-Order / item No. 33803

www.wipesplus.com

NDC 67151-303-09

WIPES PLUS®

Re-Order / Item No. 37502

1500 CT